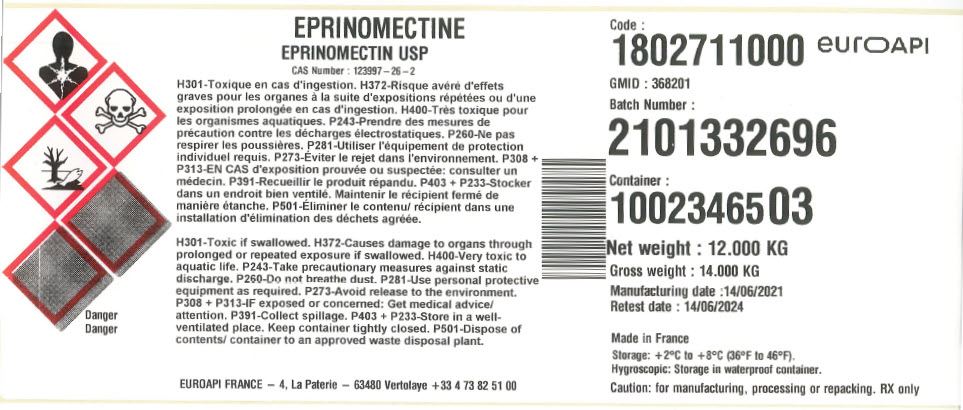 DRUG LABEL: Eprinomectine
NDC: 82298-124 | Form: POWDER
Manufacturer: EUROAPI France
Category: other | Type: BULK INGREDIENT - ANIMAL DRUG
Date: 20220316

ACTIVE INGREDIENTS: EPRINOMECTIN 1 kg/1 kg

EPRINOMECTIN USP

PRINCIPAL DISPLAY PANEL - Shipping Label

EPRINOMECTIN USP
CAS Number : 123997 – 26 – 2

H301-Toxic if swallowed. H372-Causes damage to organs through
prolonged or repeated exposure if swallowed. H400-Very toxic to
aquatic life. P243-Take precautionary measures against static
discharge. P260-Do not breathe dust. P281-Use personal protective
equipment as required. P273-Avoid release to the environment.
P308 + P313-IF exposed or concerned: Get medical advice/
attention. P391-Collect spillage. P403 + P233-Store in a well-
ventilated place. Keep container tightly closed. P501-Dispose of
contents/ container to an approved waste disposal plant.

Danger

EUROAPI FRANCE – 4, La Paterie – 63480 Vertolaye +33 4 73 82 51 00

Code :
1802711000 euroAPI
GMID : 368201
Batch Number :
2101332696
Container :
1002346503

Net weight : 12.000 KG
Gross weight : 14.000 KG
Manufacturing date :14/06/2021
Retest date : 14/06/2024

Made in France
Storage: +2°C to +8°C (36°F to 46°F).
Hygroscopic: Storage in waterproof container.

Caution: for manufacturing, processing or repacking. RX only